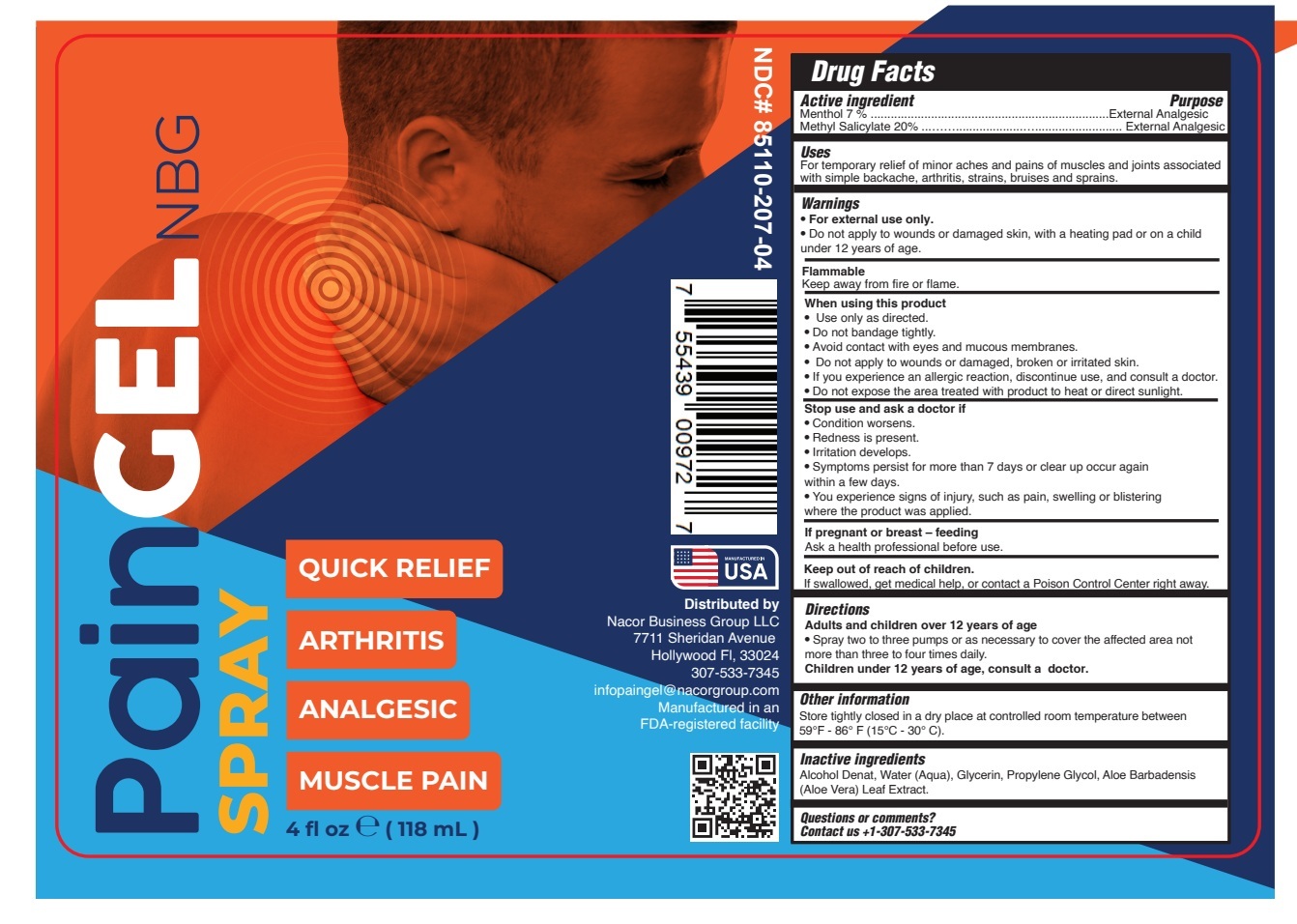 DRUG LABEL: PAINGEL
NDC: 85110-207 | Form: SPRAY
Manufacturer: NACOR BUSINESS GROUP LLC
Category: otc | Type: HUMAN OTC DRUG LABEL
Date: 20260218

ACTIVE INGREDIENTS: MENTHOL 7 g/100 mL; METHYL SALICYLATE 20 g/100 mL
INACTIVE INGREDIENTS: WATER; ALCOHOL; PROPYLENE GLYCOL; GLYCERIN; ALOE BARBADENSIS LEAF JUICE

85110-207-04

ACTIVE INGREDIENT

Menthol 7%

Methyl Salicylate 20%

PURPOSE

External Analgesic

USE

For temporary relief of minor aches and pains of muscles and joints associated with simple backache, arthritis, strains, bruises and sprains.

WARNINGS

- For external use only.
- Do not apply to wounds or damaged skin, with a heating pad or on a child under 12 years of age.

Flammable

Keep away from fire or flame.

WHEN USING

- Use only as directed.
- Do not bandage tightly.
- Avoid contact with eyes and mucous membranes.
- If you experience an allergic reaction, discontinue use, and consult a doctor.
- Do not expose the area treated with product to heat or direct sunlight.

Stop use and ask a doctor if

- Condition worsens.
- Redness is present.
- Irritation develops.
- Symptoms persist for more than 7 days or clear up occur again within a few days.
- You experience signs of injury, such as pain, swelling or blistering where the product was applied.

If pregnant or breast – feeding

Ask a health professional before use.

KEEP OUT OF REACH OF CHILDREN

If swallowed, get medical help, or contact a Poison Control Center right away.

Directions

Adults and Children over 12 years of age

Spray two to three pumps or as necessary to cover the affected area not more than three to four times daily.

Children under 12 years of age: do not use, consult a doctor.

Other information

Store tightly closed in a dry place at controlled room temperature between 59°F - 86° F (15°C - 30° C).

INACTIVE INGREDIENT

Alcohol Denat, Water (Aqua), Glycerin, Propylene Glycol, Aloe Barbadensis (Aloe Vera) Leaf Juice.

Questions or comments?

Contact us +1-307-533-7345